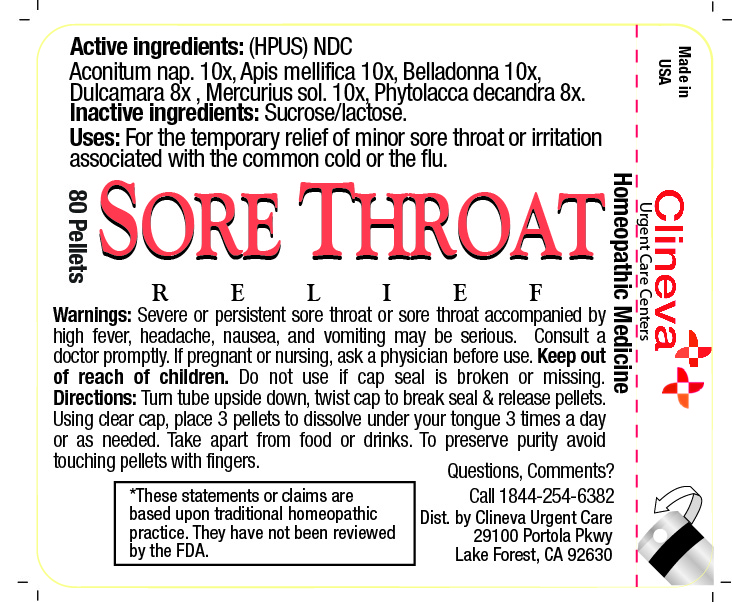 DRUG LABEL: Sore Throat Relief
NDC: 71409-311 | Form: PELLET
Manufacturer: Clineva Urgent Care
Category: homeopathic | Type: HUMAN OTC DRUG LABEL
Date: 20180105

ACTIVE INGREDIENTS: APIS MELLIFERA 10 [hp_X]/1 1; ATROPA BELLADONNA 10 [hp_X]/1 1; ACONITUM NAPELLUS 10 [hp_X]/1 1; PHYTOLACCA AMERICANA ROOT 8 [hp_X]/1 1; MERCURIUS SOLUBILIS 10 [hp_X]/1 1; SOLANUM DULCAMARA WHOLE 8 [hp_X]/1 1
INACTIVE INGREDIENTS: LACTOSE; SUCROSE

SORE THROAT RELIEF

Directions

Turn tube upside down, twist cap to break seal & release pellets. Using clear cap, place 3 pellets to dissolve under your tongue 3 times a day or as needed. Take apart from food or drinks. To preserve purity avoid touching pellets with fingers.

Active ingredients:

(HPUS) Homeopathic Medicine

Aconitum nap. 10X, Apis mellifica 10X, Belladonna 10X, Dulcamara 8X, Mercurius sol. 10X, Phytolacca decandra 8X

Uses:

For the temporary relief of minor sore throat or irritation associated with the common cold or the flu.

Warnings:

Severe or persistent sore throst or sore throat accompanied by high fever, headache, nausea, and vomitting may be serious. Consult a doctor promptly. If pregnant or nursing, ask a physician before use. Do not use if cap seal is broken or missing.

Inactive ingredients:

Sucrose/lactose

Questions, Comments?

Call 1-844-254-6382

Dist. by Clineva Urgent Care

29100 Portola Pkwy

Lake Forest, CA 92630

INDICATIONS AND USAGE

Uses: For the temporary relief of minor sore throat or irritation associated with the common cold or the flu.